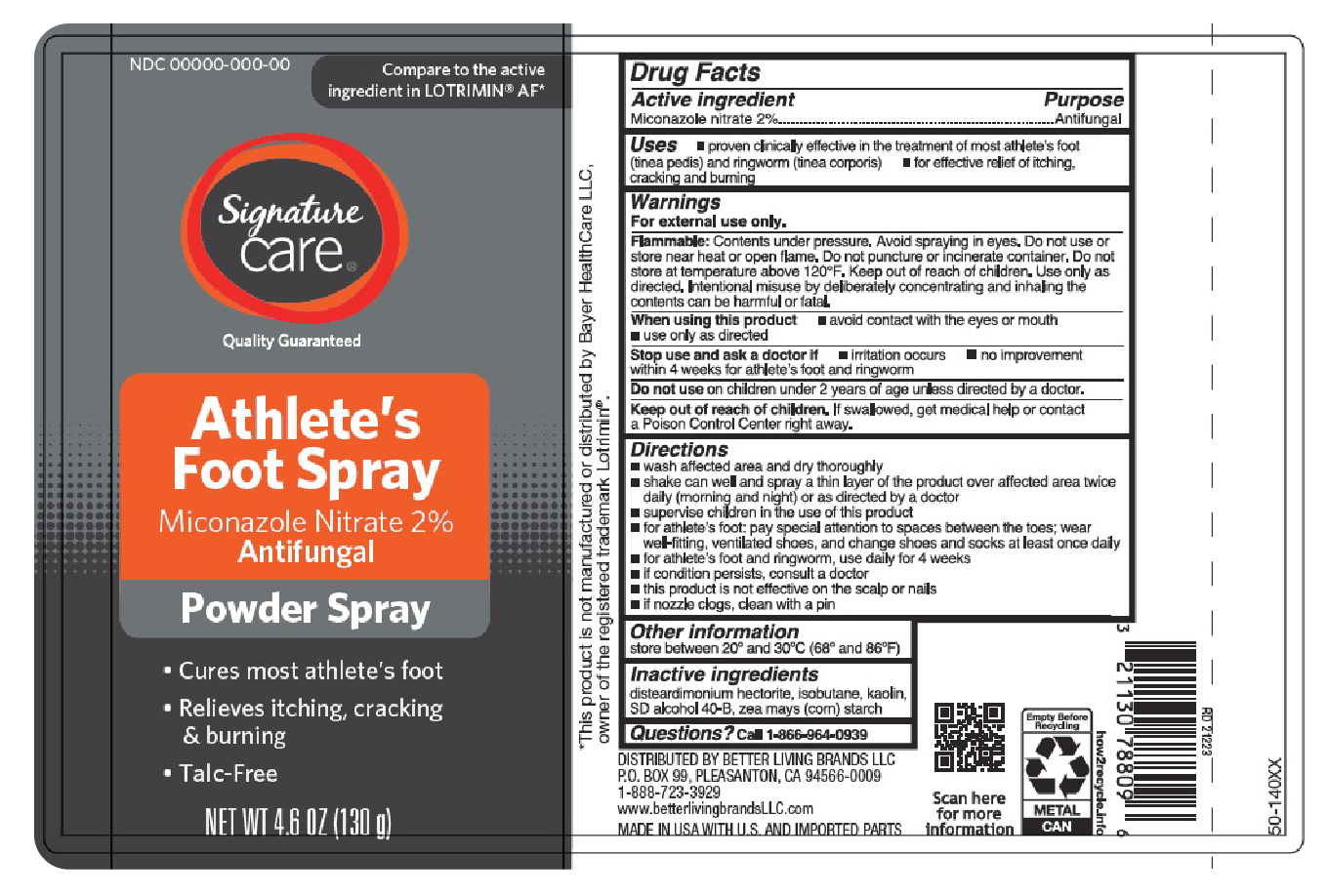 DRUG LABEL: Miconazole Nitrate
NDC: 21130-212 | Form: AEROSOL, SPRAY
Manufacturer: Better Living Brands
Category: otc | Type: HUMAN OTC DRUG LABEL
Date: 20251209

ACTIVE INGREDIENTS: MICONAZOLE NITRATE 2.6 g/130 g
INACTIVE INGREDIENTS: DISTEARDIMONIUM HECTORITE; STARCH, CORN; KAOLIN; ALCOHOL; ISOBUTANE

Albertsons - Signature Care Miconazole Powder Spray

Active ingredient

Miconazole nitrate 2%

Purpose

Antifungal

Uses

- proven clinically effective in the treatment of most athlete’s foot (tinea pedis) and ringworm (tinea corporis)
- for effective relief of itching, cracking and burning

Warnings

For external use only.

Flammable:

Contents under pressure. Avoid spraying in eyes. Do not use or store near heat or open flame. Do not puncture or incinerate container. Do not store at temperature above 120°F. Keep out of reach of children. Use only as directed. Intentional misuse by deliberately concentrating and inhaling the contents can be harmful or fatal.

When using this product

- avoid contact with the eyes or mouth
- use only as directed

Stop use and ask a doctor if

- irritation occurs
- no improvement within 4 weeks for athlete’s foot and ringworm

Do not use

on children under 2 years of age unless directed by a doctor.

Keep out of reach of children.

If swallowed, get medical help or contact a Poison Control Center right away.

Directions

- wash affected area and dry thoroughly
- shake can well and spray a thin layer of the product over affected area twice daily (morning and night) or as directed by a doctor
- supervise children in the use of this product
- for athlete’s foot: pay special attention to spaces between the toes; wear well-fitting, ventilated shoes, and change shoes and socks at least once daily
- for athlete’s foot and ringworm, use daily for 4 weeks
- if condition persists, consult a doctor
- this product is not effective on the scalp or nails
- if nozzle clogs, clean with a pin

Other information

store between 20º and 30ºC (68ºF and 86º)

Inactive ingredients

disteardimonium hectorite, isobutane, kaolin, SD alcohol 40-B, zea mays (corn) starch

Questions?

Call 1-866-964-0939

Principal Display Panel

Signature

Care

Athlete's

Foot Spray

Miconazole Nitrate 2%

Antifungal

Powder Spray

- Cures most athlete's foot
- Relieves itching, cracking

& burning

- Talc-free

NET WT 4.6 OZ (130 g)